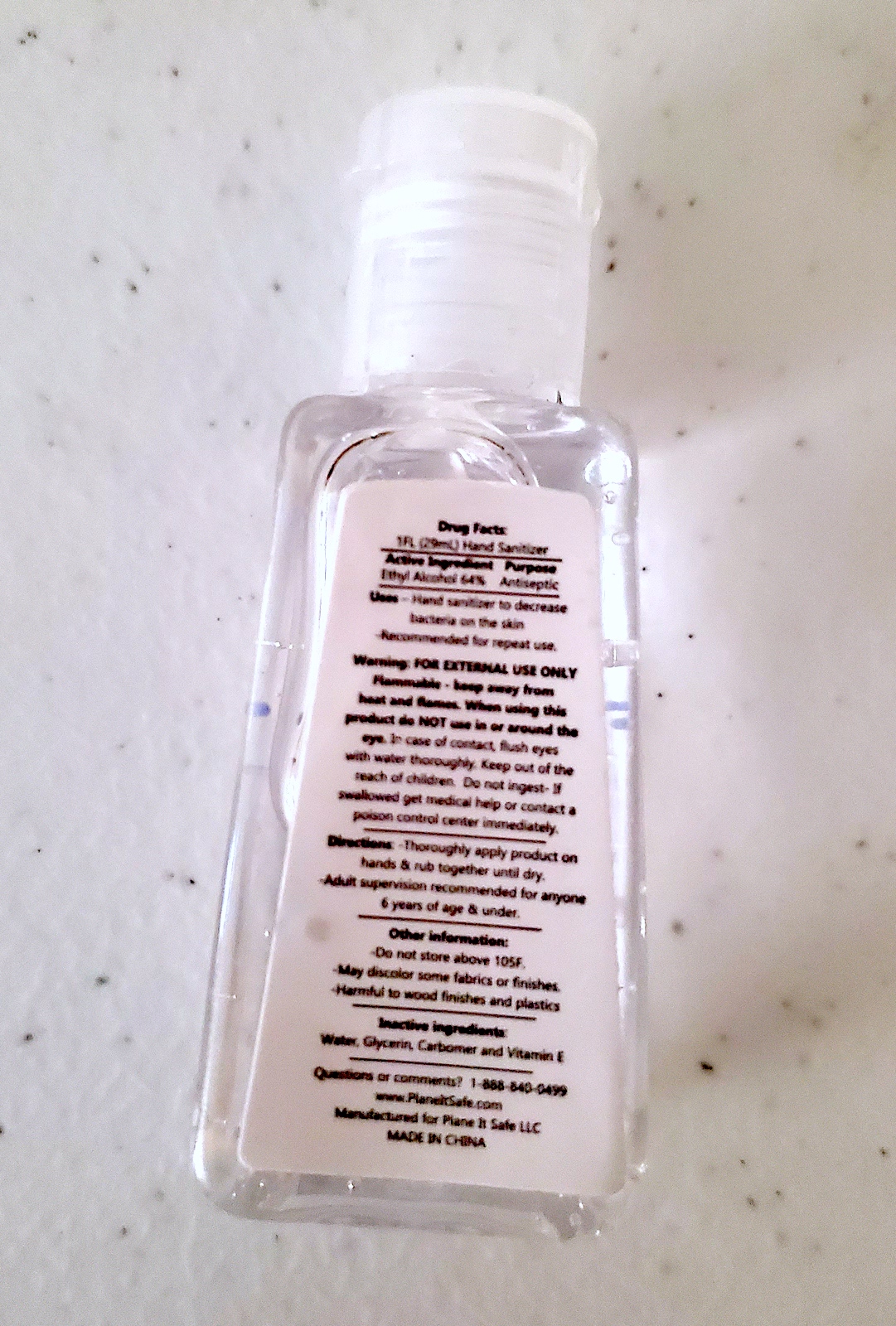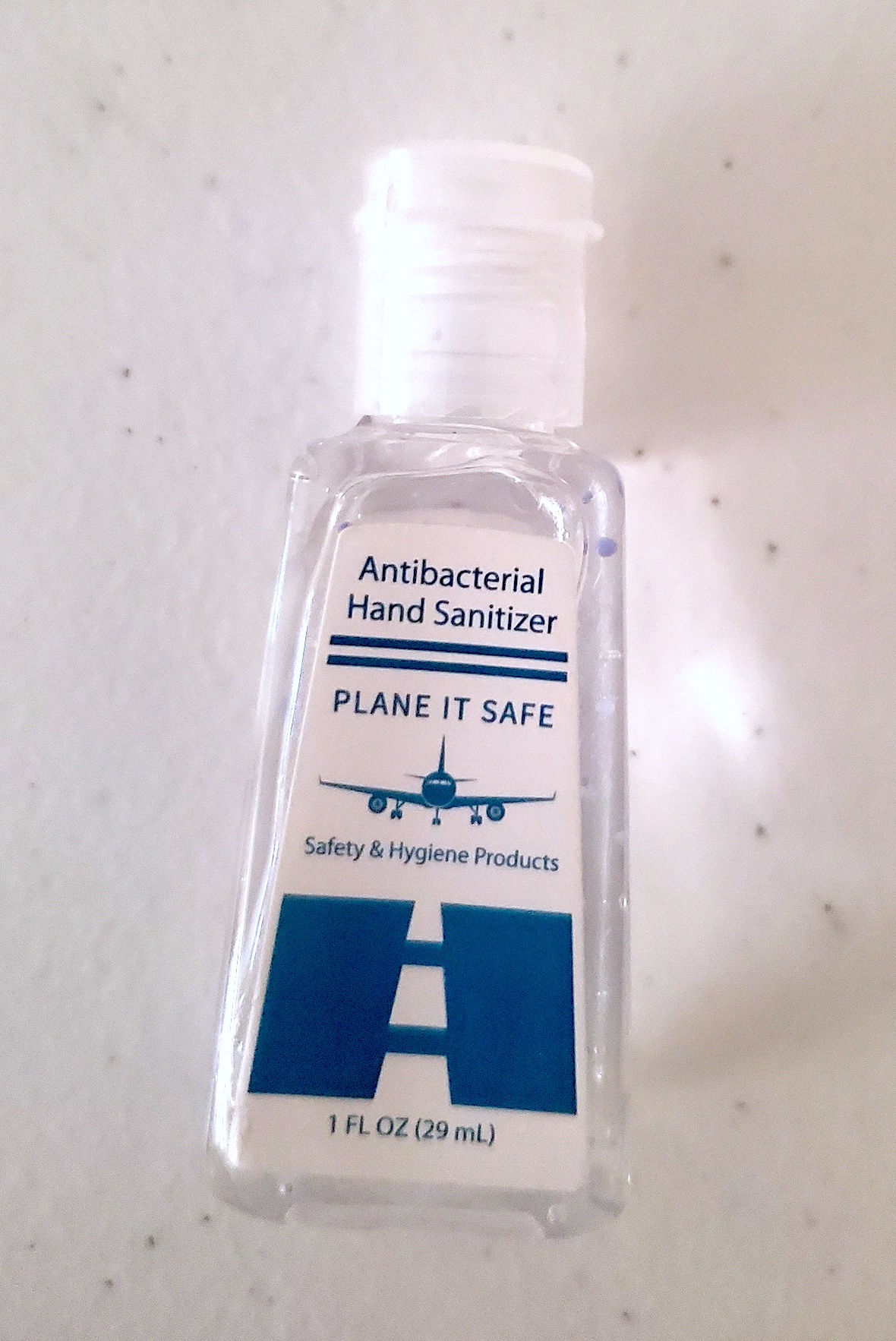 DRUG LABEL: Plane It Safe Hand Sanitizer
NDC: 72920-2012 | Form: GEL
Manufacturer: Plane It Safe LLC
Category: otc | Type: HUMAN OTC DRUG LABEL
Date: 20200504

ACTIVE INGREDIENTS: ALCOHOL 64 mL/100 mL
INACTIVE INGREDIENTS: WATER

Plane It Safe Hand Sanitizer

WARNINGS

External Use Only

ACTIVE INGREDIENT

Ethyl Alcohol 64%

KEEP OUT OF REACH OF CHILDREN

Keep out of the reach of children. Adult supervision for children under 6 years old

Stop use if redness or rash persists longer than 72 hours

PURPOSE

To reduce bacteria on the hands

DOSAGE AND ADMINISTRATION

Apply throughly on hands and rub together until dry

INACTIVE INGREDIENT

Water, Aloe Barbadensis Leaf Juice, Glycerin, Propylene, Glycol, Carbomer, Triethanolamine, Fragrance

INDICATIONS AND USAGE

Use as directed

WHEN USING

Use to reduce bacteria on the hands